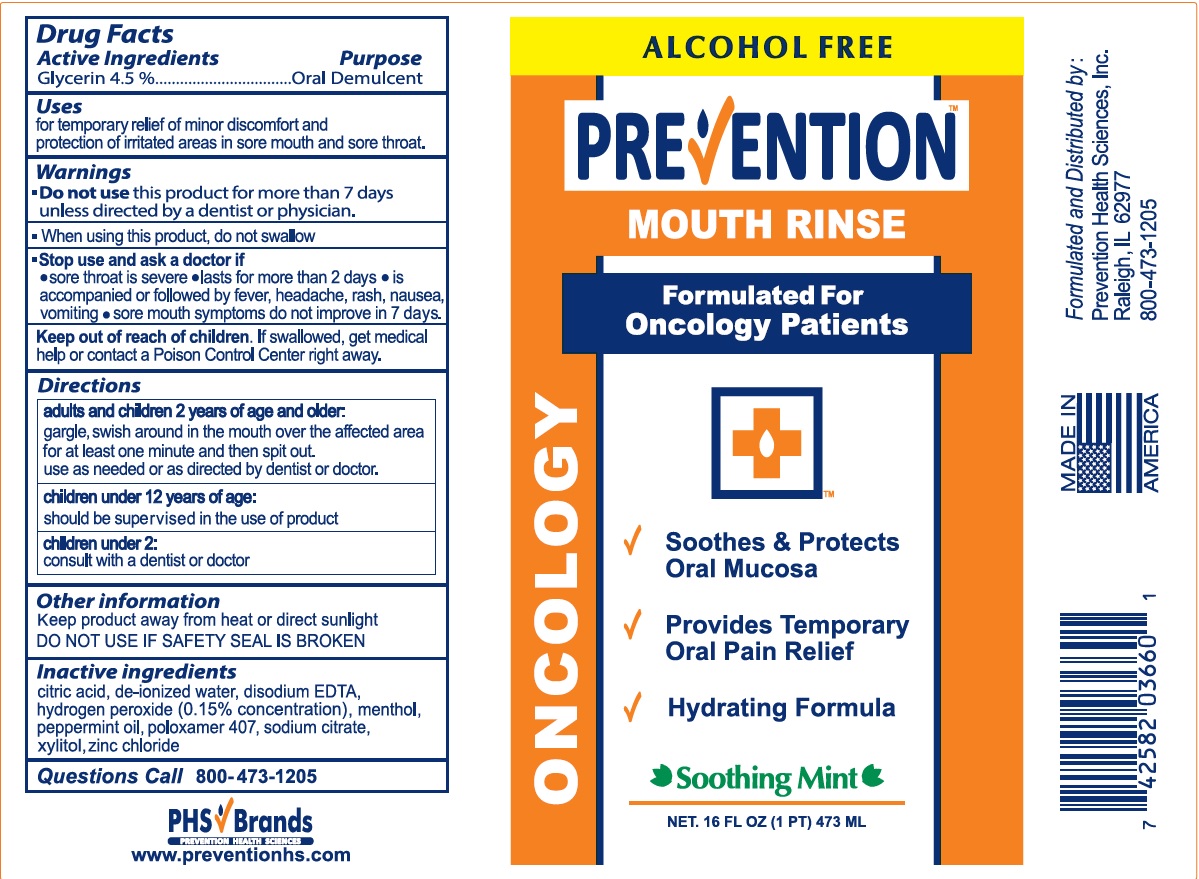 DRUG LABEL: Prevention Oncology Mouth Rinse
NDC: 69951-001 | Form: LIQUID
Manufacturer: Prevention Health Sciences, Inc.
Category: otc | Type: HUMAN OTC DRUG LABEL
Date: 20250101

ACTIVE INGREDIENTS: GLYCERIN 4.5 mg/100 mL
INACTIVE INGREDIENTS: CITRIC ACID MONOHYDRATE; WATER; EDETATE DISODIUM; HYDROGEN PEROXIDE; MENTHOL; PEPPERMINT OIL; POLOXAMER 407; SODIUM CITRATE; ZINC CHLORIDE; XYLITOL

Prevention Oncology Mouth Rinse

Active Ingredients

Glycerin 4.5%

Purpose

Oral Demulcent

Uses

for temporary relief of minor discomfort and protection of irritated areas in sore mouth and sore throat.

Do not use this product for more than 7 days unless directed by a dentist or physician

When using this product, do not swallow.

Stop use and ask a doctor if

• sore throat is severe • lasts for more than 2 days • is accompanied or followed by fever, headache, rash, nausea or vomiting • sore mouth symptoms do not improve in 7 days

Keep out of reach of children. If swallowed, get medical help or contact a Poison Control Center right away.

Directions

adults and children 2 years of age and older: gargle, swish around in the mouth over the affected area for at least one minute and then spit out. Use as needed or as directed by dentist or doctor.

children under 12 years of age should be supervised in the use of product.

children under 2: consult with a dentist or doctor.

Other information

keep product away from heat or direct sunlight

DO NOT USE IF SAFETY SEAL IS BROKEN

Inactive ingredients

citric acid, de-ionized water, disodium EDTA, hydrogen peroxide (0.15% concentration), menthol, peppermint oil, poloxamer 407, sodium citrate, xylitol, zinc chloride

Questions Call 800-473-1205

Formulated and Ditributed by:

Prevention Health Sciences, Inc.

Raleigh, IL 62977

800-473-1205

PHS Brands

www.preventionhs.com

PACKAGE LABEL

ALCOHOL FREE

PREVENTION MOUTH RINSE

Formulated for Oncology Patients

√ Soothes & Protects Oral Mucosa

√ Provides Temporary Oral Pain Relief

√ Hydrating Formula

Soothing Mint

NET. 16 FL OZ (1 PT) 473 ML